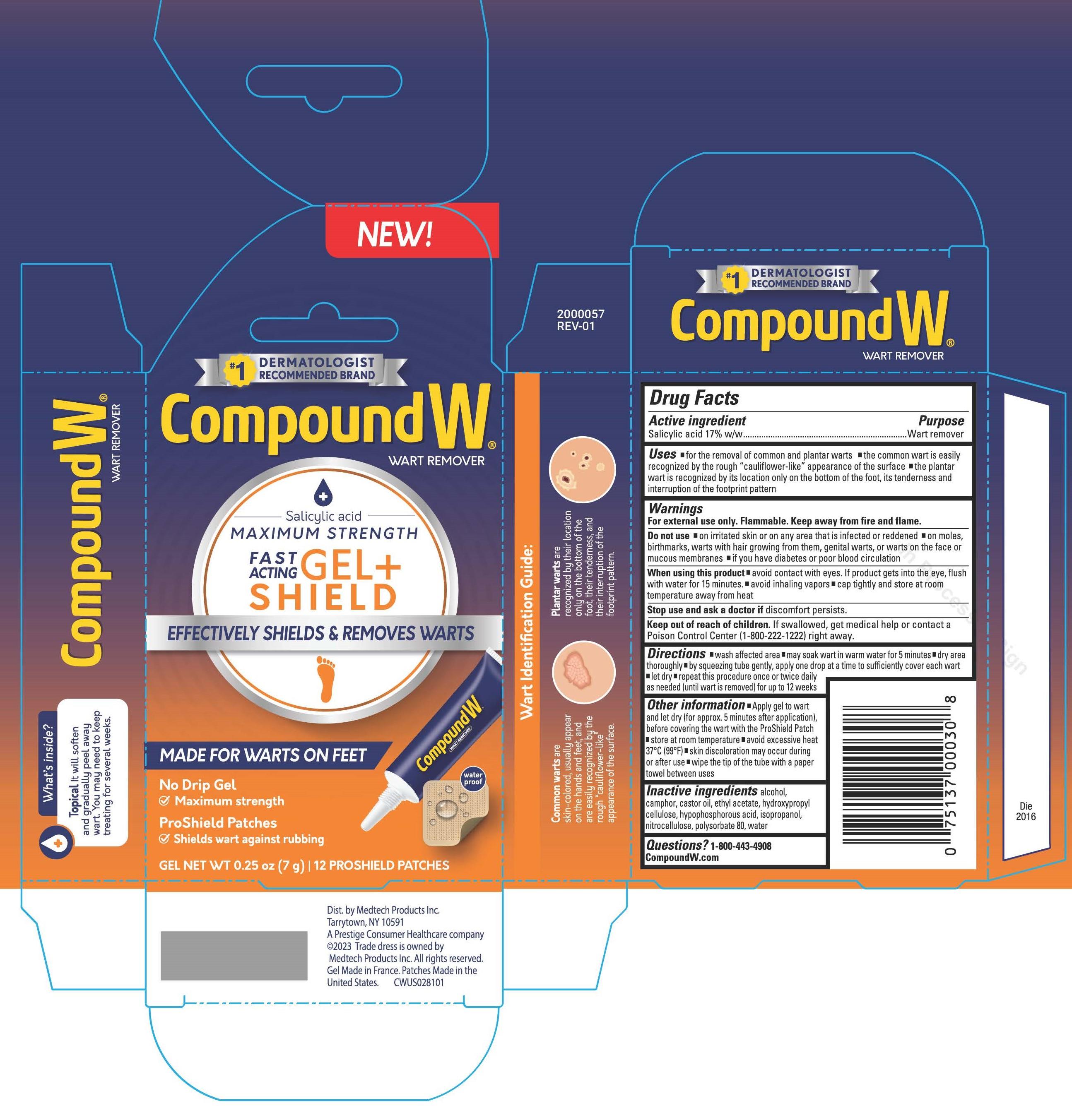 DRUG LABEL: Compound W
NDC: 51142-595 | Form: GEL
Manufacturer: ASO LLC
Category: otc | Type: HUMAN OTC DRUG LABEL
Date: 20231115

ACTIVE INGREDIENTS: SALICYLIC ACID 170 mg/1 g
INACTIVE INGREDIENTS: ETHYL ACETATE; CAMPHOR (NATURAL); CASTOR OIL; HYPOPHOSPHOROUS ACID; POLYSORBATE 80; ALCOHOL; HYDROXYPROPYL CELLULOSE (1600000 WAMW); ISOPROPYL ALCOHOL; PYROXYLIN; WATER

COMPOUND W WART REMOVER SALICYLIC ACID MAXIMUM STRENGTH FAST ACTING GEL + SHIELD

ACTIVE INGREDIENT

Salicylic acid 17% w/w

PURPOSE

Wart remover

USE

- for the removal of common and plantar warts.
- the common wart is easily recognized by the rough “cauliflower-like” appearance on the surface.
- the plantar wart is recognized by its location only on the bottom of the foot, its tenderness, and the interruption of the footprint pattern.

WARNINGS

For external use only.

Flammable. Keep away from fire and flame.

Do not use

- on irritated skin or on any area that is infected or reddened.
- on moles, birthmarks, warts with hair growing from them, genital warts or warts on the face or mucous membranes.
- if you have diabetes or poor blood circulation.

When using this product

- avoid contact with eyes. If product gets into the eye, flush with water for 15 minutes.
- avoid inhaling vapors
- cap tightly and store at room temperature away from heat

Stop use and ask a doctor if

discomfort persists.

Keep out of reach of children.

If swallowed, get medical help or contact a Poison Control Center (1-800-222-1222) right away.

DIRECTIONS

- wash affected area
- may soak wart in warm water for 5 minutes
- dry area thoroughly
- by squeezing tube gently, apply one drop at a time to sufficiently cover each wart
- let dry
- repeat this procedure once or twice daily as needed (until wart is removed) for up to 12 weeks

OTHER INFORMATION

- Apply gel to wart and let dry (for approx. 5 minutes after application), before covering the wart with the ProShield Patch.
- store at room temperature
- avoid excessive heat 37C (99F)
- skin discoloration may accur during or after use
- wipe the tip of the tube with a paper towel between uses

INACTIVE INGREDIENTS

alcohol, camphor, castor oil, ethyl acetate, hydroxypropyl cellulose, hypophosphorous acid, isopropanol, nitrocellulose, polysorbate 80, water

QUESTIONS?

1-800-443-4908

CompoundW.com

PRINCIPAL DISPLAY PANEL

Compound W

WART REMOVER

Salicylic acid

MAXIMUM STRENGTH

FAST ACTING GEL + SHIELD

EFFECTIVELY SHIELDS & REMOVES WARTS

MADE FOR WARTS ON FEET

No Drip Gel

- Maximum strength

ProShield Patches

- Shields wart against rubbing

GEL NET WT 0.25 oz (7 g) I 12 PROSHIELD PATCHES